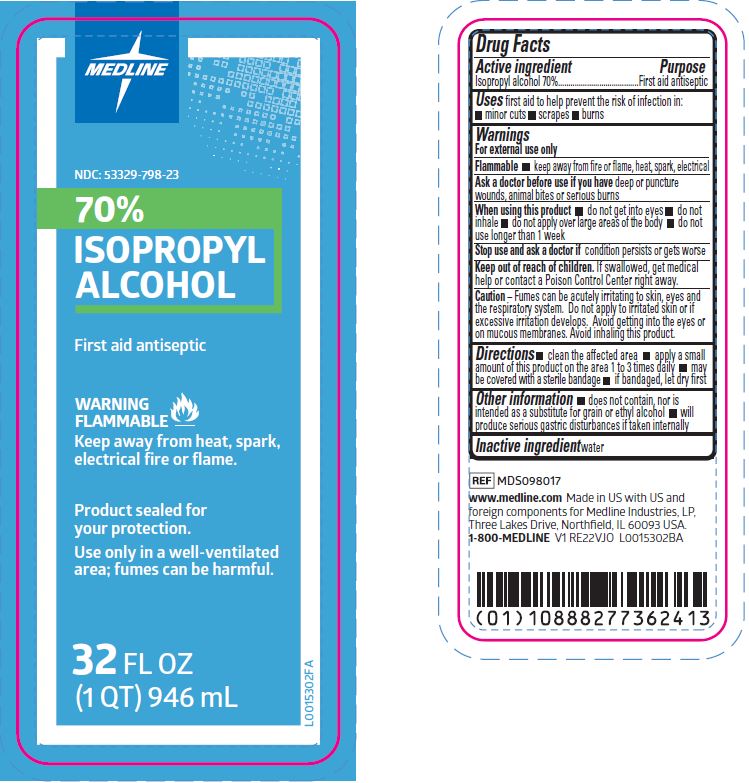 DRUG LABEL: Isopropyl Alcohol
NDC: 53329-798 | Form: LIQUID
Manufacturer: Medline Industries, LP
Category: otc | Type: HUMAN OTC DRUG LABEL
Date: 20260211

ACTIVE INGREDIENTS: ISOPROPYL ALCOHOL 70 mL/100 mL
INACTIVE INGREDIENTS: WATER

798 Medline 70% Isopropyl Alcohol First Aid Antiseptic

Active ingredient

Isopropyl Alcohol 70%

Purpose

First Aid Antiseptic

Uses

For first aid to help prevent the risk of infection in minor:

- Minor cuts
- scrapes
- burns

Warnings

For external use only.

Flammable. Keep away from fire or flame, heat, spark, electrical

Ask a doctor before use if you have

Deep or puncture wounds, animal bites or serious burns.

When using this product

- do not get into eyes
- Do not inhale
- Do not apply over large ares of the body
- Do not use longer than 1 week

Stop use and ask a doctor if

condition persists or gets worse

Keep out of reach of children.

If swallowed, get medical help or contact a Poison Control Center right away.

Caution

Fumes can be acutely irritating to skin, eyes, and the respiratory system. Do not apply to irritated skin or if excessive irritation develops. Avoid getting into the eyes or on mucous membranes. Avoid inhaling this product

Directions

- Clean the affected area.
- Apply a small amount of the product on the area 1 to 3 times daily.
- May be covered with a sterile bandage.
- If bandaged, let dry first.

Other Information

- Does not contain, nor is intended as a substitute for grain or ethyl alcohol.
- Will produce serious gastric disturbances if taken internally.

Inactive ingredients

Water

Manufacturing Information

www.medline.com

Made in US with US and foreign components
for Medline Industries, LP
Three Lakes Drive, Northfield, IL 60093 USA
1-800-MEDLINE

REF: MDS098017